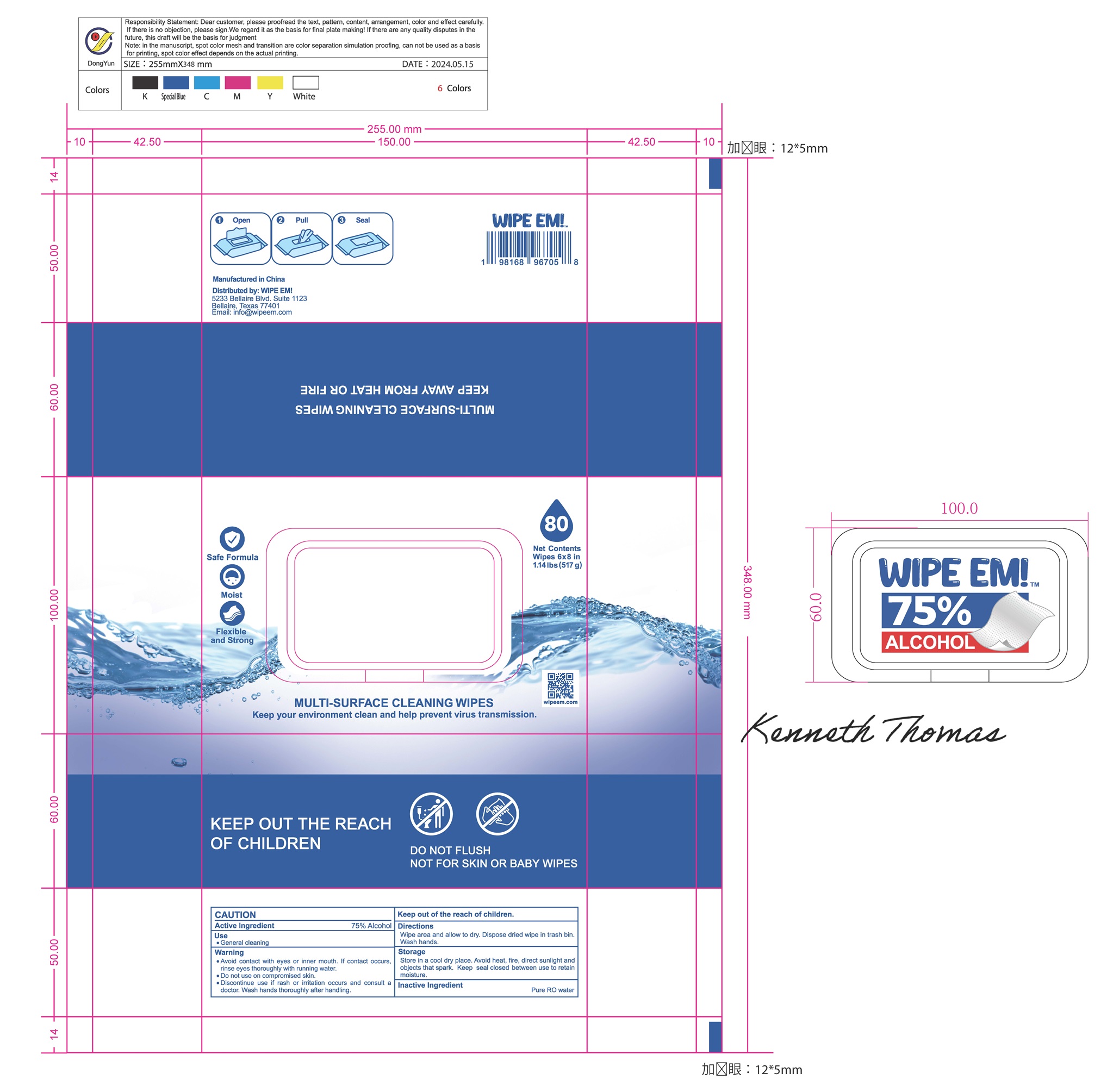 DRUG LABEL: Alcohol Wipes
NDC: 81079-003 | Form: CLOTH
Manufacturer: Shaoxing Elite Bio-Tech Co., Ltd.
Category: otc | Type: HUMAN OTC DRUG LABEL
Date: 20240808

ACTIVE INGREDIENTS: ALCOHOL 75 mL/100 mL
INACTIVE INGREDIENTS: WATER

Active ingredient

Alcohol 75%

Inactive ingredients

water

Warnings

- Avoid contact with eyes or inner mouth. If contact occurs, rinse eyes thoroughly with running water.

- Do not use on compromised skin.

- Discontinue use if rash or irritation occurs and consult a doctor. Wash hands thoroughly after handling.

- Keep out of reach of children

Keep out of reach of children

ASK DOCTOR/PHARMACIST

Discontinue use if rash or irritation occurs and consult a doctor.

Do not use on compromised skin.

When using this product, avoid contact with eyes and mouth. If products get in the eyes, flush thoroughly with water.

DOSAGE AND ADMINISTRATION

Wipe skin area and allow to dry with one to two pieces each time.

DISPOSAL AND WASTE HANDLING

Dispose dired wipe in trash bin.

INDICATIONS AND USAGE

General skin cleaning

PURPOSE

General skin cleaning